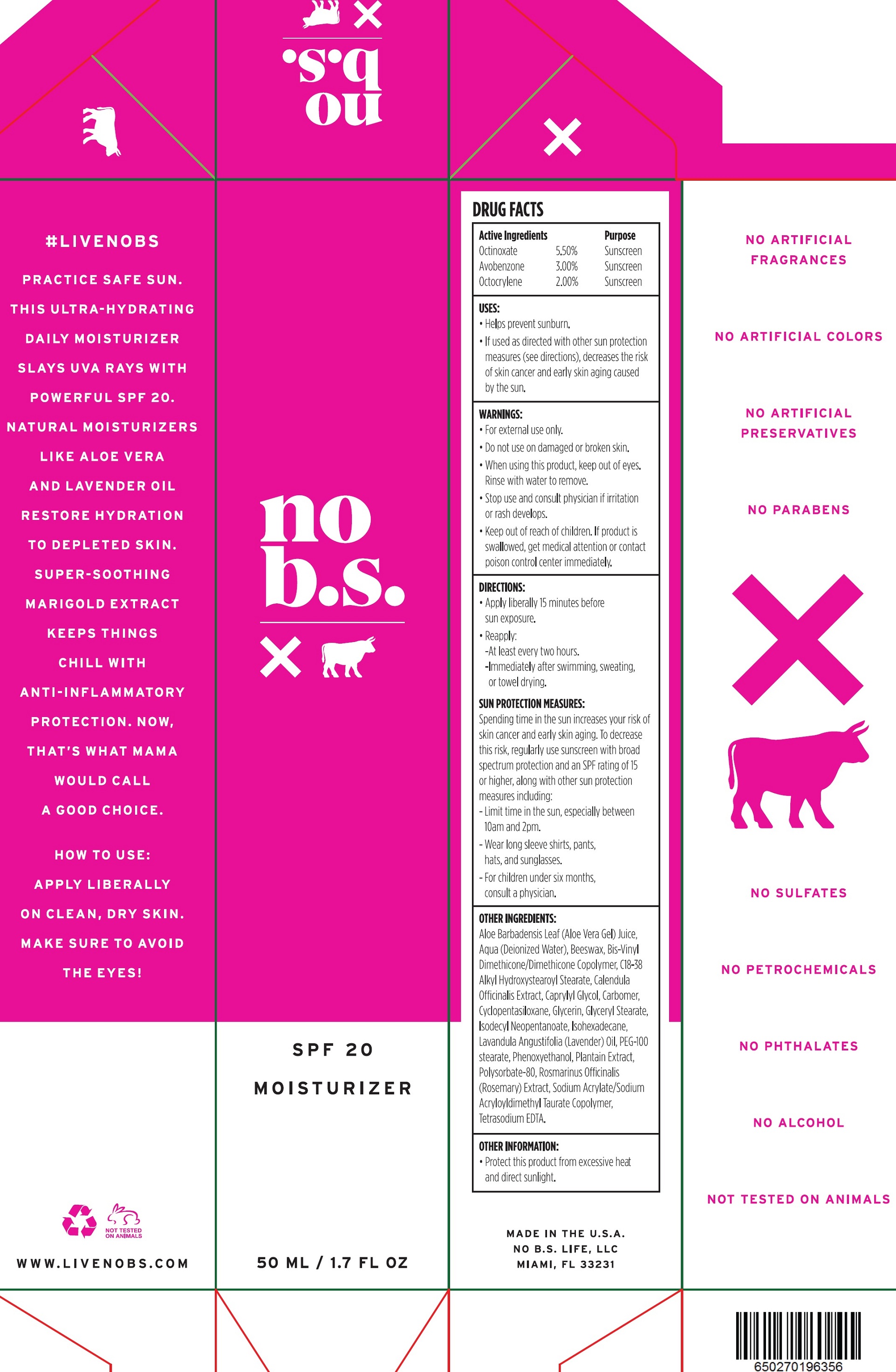 DRUG LABEL: No BS SPF20 Moisturizer
NDC: 71852-060 | Form: CREAM
Manufacturer: Product Management LLC
Category: otc | Type: HUMAN OTC DRUG LABEL
Date: 20231111

ACTIVE INGREDIENTS: OCTINOXATE 55 mg/1 mL; AVOBENZONE 30 mg/1 mL; OCTOCRYLENE 20 mg/1 mL
INACTIVE INGREDIENTS: ALOE VERA LEAF; WATER; YELLOW WAX; CALENDULA OFFICINALIS FLOWER; CAPRYLYL GLYCOL; CARBOXYPOLYMETHYLENE; CYCLOMETHICONE 5; GLYCERIN; GLYCERYL MONOSTEARATE; ISODECYL NEOPENTANOATE; ISOHEXADECANE; LAVENDER OIL; PEG-100 STEARATE; PHENOXYETHANOL; POLYSORBATE 80; ROSEMARY; SODIUM ACRYLATE/SODIUM ACRYLOYLDIMETHYLTAURATE COPOLYMER (4000000 MW); EDETATE SODIUM

No BS SPF20 Moisturizer

Active Ingredients

Octinoxate 5.50%

Avobenzone 3.00%

octocrylene 2.00%

Purpose

Sunscreen

Uses

- Helps preven sunburn.
- If used as directed with other sun protection measures (see directions), decreases the risk of skin cancer and early skin aging caused by the sun.

Warnings:

- For external use only.

Do not use

- on damaged or broken skin

When using this product,

- keep out of eyes. Rinse with water to remove.

Stop use and consult physician

- if irritation or rash develops.

Keep out of reach of children.

- If product is swallowed, get medical attention or contact poison control center immediately.

Directions:

- Apply liberally 15 minutes before sun exposure.
- Reapply:
- At least every two hours.
- Immediately after swimming, sweating, or towel drying.

SUN PROTECTION MEASURES:

Spending time in the sun increases your risk of skin cancer abnd early skin aging. To decrease this risk, regularly use sunscreen with broad spectrum protection and an SPF rating of 15 or higher, along with other sun protection measures including:

- Limit time in the sun, especially between 10am and 2pm.

- Wear long sleeve shirts, pants, hats and sunglasses.

- For children under six months, consult a physician.

Inactive Ingredients:

Aloe Barbadensis Leaf (Aloe Vera Gel) Juice, Aqua (Deionized Water), Beeswax, Bis-Vinyl Dimethicone/Dimethicone Copolymer, C18-38 Alkyl Hydroxystearoyl Stearate, Calendula Officinalis Extract, Caprylyl Glycol, Carbomer, Cyclopentasiloxane, Glycerin, Glyceryl Stearate, Isodecyl Neopentanoate, Isohexadecane, Lavandula Angustifolia (Lavender) Oil, PEG-100 Stearate, Phenoxyethanol, Plantain Extract, Polysorbate-80, Rosmarinus Officinalis (Rosemary) Extract, Sodium Acrylate/Sodium Acryloyldimethyl Taurate Copolymer, Tetrasodium EDTA.

OTHER INFORMATION:

- Protect this product from excessive heat and direct sunlight.